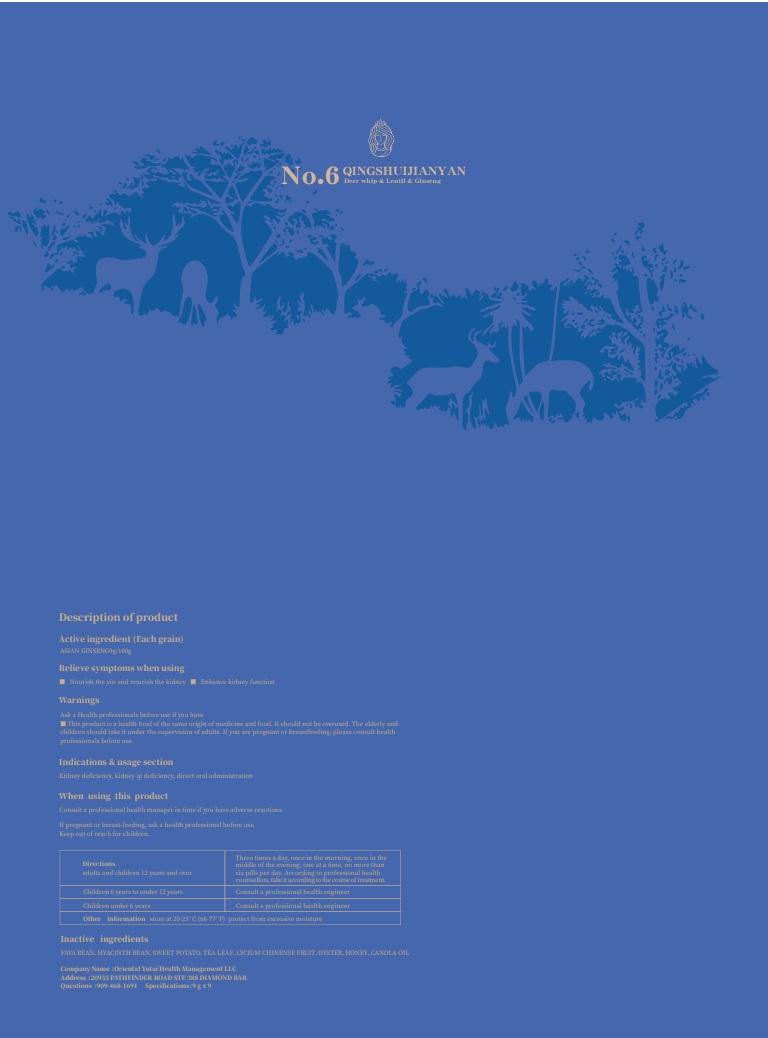 DRUG LABEL: broad bean and ginseng cake
NDC: 83494-003 | Form: OINTMENT, AUGMENTED
Manufacturer: Oriental Yutai Health Management LLC
Category: homeopathic | Type: HUMAN OTC DRUG LABEL
Date: 20230602

ACTIVE INGREDIENTS: ASIAN GINSENG 9 g/100 g
INACTIVE INGREDIENTS: HYACINTH BEAN; LYCIUM CHINENSE FRUIT; CANOLA OIL; TEA LEAF; HONEY; SWEET POTATO; FAVA BEAN; OYSTER, UNSPECIFIED

Active ingredients

ASIAN GINSENG 9% w/w.

Relieve symptoms when using

■ Nourish the yin and nourish the kidney■ Enhance kidney function

Indications & usage section

Blood vessel blockage, hypertension, hyperglycaemia, direct oral administration

Warnings

Ask a Health professionals before use if you have

■This product is a health food of the same origin of medicine and food. It should not be overused. The elderly and children should take it under the supervision of adults. If you are pregnant or breastfeeding, please consult health professionals before use.

Keep out of reach for children.

When using this product

Consult a professional health manager in time if you have adverse reactions.
If pregnant or breast-feeding, ask a health professional before use.

Directions

adults and children 12 years and over

three times a day, once in the morning, once in the middle of the evening, one at a time, no more than six pills per day. According to professional health counsellors, take it according to the course of treatment.

children 6 years to under 12 years

Consult a professional health engineer

children under 6 years

Consult a professional health engineer

Inactive ingredients

FAVA BEAN、HYACINTH BEAN、SWEET POTATO、TEA LEAF、LYCIUM CHINENSE FRUIT、OYSTER、HONEY、CANOLA OIL